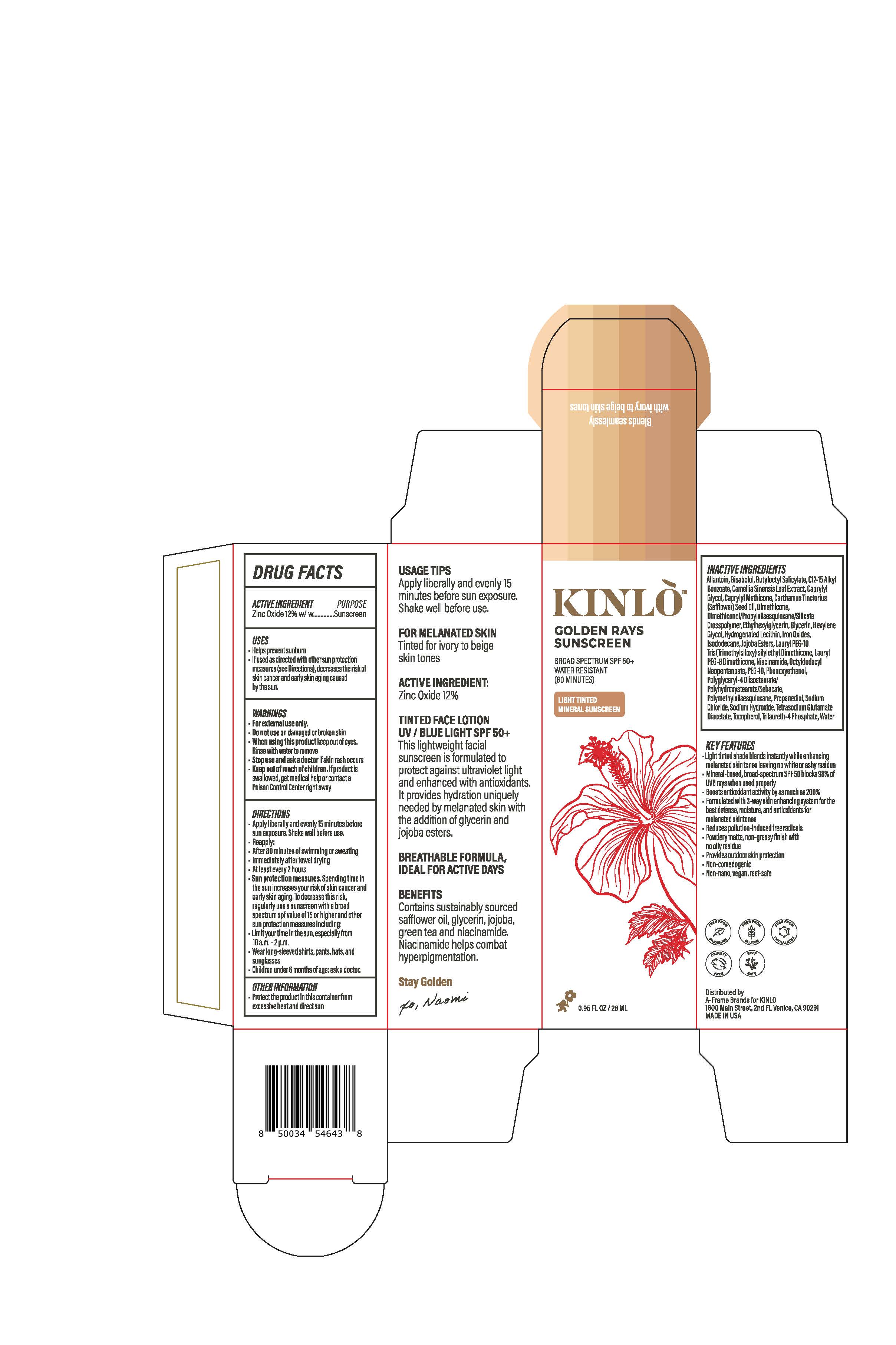 DRUG LABEL: Golden Rays Sunscreen (Light Tinted)
NDC: 82184-1351 | Form: LOTION
Manufacturer: A-Frame SunCo Inc
Category: otc | Type: HUMAN OTC DRUG LABEL
Date: 20250109

ACTIVE INGREDIENTS: ZINC OXIDE 132 mg/1 mL
INACTIVE INGREDIENTS: DIMETHICONOL/PROPYLSILSESQUIOXANE/SILICATE CROSSPOLYMER (450000000 MW); PROPANEDIOL; TETRASODIUM GLUTAMATE DIACETATE; SODIUM CHLORIDE; PHENOXYETHANOL; POLYMETHYLSILSESQUIOXANE (4.5 MICRONS); GLYCERIN; TOCOPHEROL; FERRIC OXIDE RED; FERRIC OXIDE YELLOW; FERROSOFERRIC OXIDE; ALLANTOIN; ALKYL (C12-15) BENZOATE; DIMETHICONE; TRILAURETH-4 PHOSPHATE; BUTYLOCTYL SALICYLATE; OCTYLDODECYL NEOPENTANOATE; ISODODECANE; .ALPHA.-BISABOLOL, (+)-; SODIUM HYDROXIDE; WATER; NIACINAMIDE; ETHYLHEXYLGLYCERIN; HEXYLENE GLYCOL

Golden Rays Sunscreen (Light Tinted)